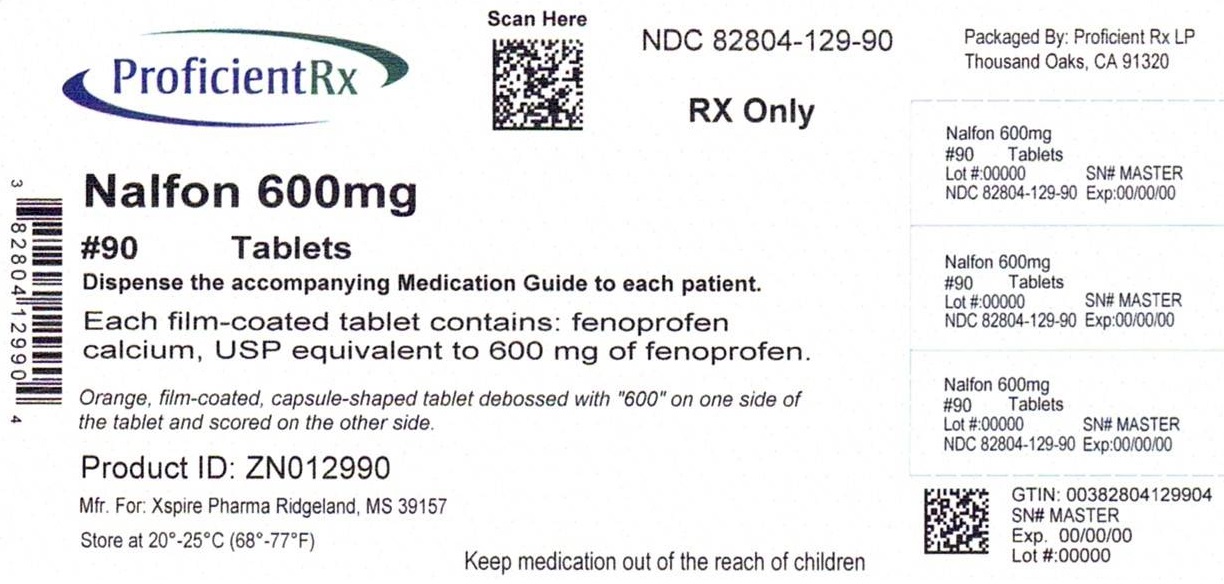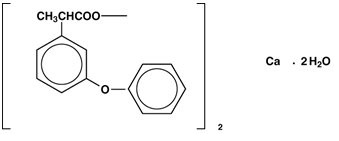 DRUG LABEL: NALFON
NDC: 82804-129 | Form: TABLET, FILM COATED
Manufacturer: Proficient Rx LP
Category: prescription | Type: HUMAN PRESCRIPTION DRUG LABEL
Date: 20240701

ACTIVE INGREDIENTS: FENOPROFEN CALCIUM 600 mg/1 1
INACTIVE INGREDIENTS: SILICON DIOXIDE; CROSCARMELLOSE SODIUM; HYPROMELLOSE, UNSPECIFIED; MAGNESIUM STEARATE; MICROCRYSTALLINE CELLULOSE; POLYETHYLENE GLYCOL, UNSPECIFIED; POLYSORBATE 80; STARCH, CORN; SODIUM LAURYL SULFATE; TITANIUM DIOXIDE; FD&C YELLOW NO. 6

NALFON ®(fenoprofen calcium tablets, USP)

BOXED WARNING

Cardiovascular Thrombotic Events

- Nonsteroidal anti-inflammatory drugs (NSAIDs) cause an increased risk of serious cardiovascular thrombotic events, including myocardial infarction and stroke, which can be fatal. This risk may occur early in treatment and may increase with duration of use (see WARNINGSand PRECAUTIONS).
- Fenoprofen calcium tablets are contraindicated in the setting of coronary artery bypass graft (CABG) surgery (see CONTRAINDICATIONSand WARNINGS).

Gastrointestinal Risk

- NSAIDs cause an increased risk of serious gastrointestinal adverse events including bleeding, ulceration and perforation of stomach or intestines, which can be fatal. These events can occur at any time during use and without warning symptoms. Elderly patients are at greater risk for serious gastrointestinal events (see WARNINGS).

DESCRIPTION

NALFON ®(fenoprofen calcium tablets) USP is a nonsteroidal, anti-inflammatory, antiarthritic drug. Chemically, fenoprofen calcium is an arylacetic acid derivative. The structural formula is as follows:

Benzeneacetic acid, α-methyl-3-phenoxy-, calcium salt (2:1)-(±)-, dihydrate

Fenoprofen calcium, USP is a white crystalline powder, soluble in alcohol (95%) to the extent of approximately 15 mg/mL at 25°C, slightly soluble in water and insoluble in benzene.

The pKa of fenoprofen calcium is 4.5 at 25°C.

Film-coated NALFON tablets for oral administration are available containing fenoprofen calcium as the dihydrate equivalent to 600 mg of fenoprofen and the following inactive ingredients: colloidal silicon dioxide, croscarmellose sodium, hypromellose, magnesium stearate, microcrystalline cellulose, polyethylene glycol, polysorbate 80, pregelatinized starch, sodium lauryl sulfate, titanium dioxide and FD&C Yellow No. 6 Aluminum Lake.

CLINICAL PHARMACOLOGY

NALFON ®tablets is a nonsteroidal, anti-inflammatory, antiarthritic drug that also possesses analgesic and antipyretic activities. Its exact mode of action is unknown, but it is thought that prostaglandin synthetase inhibition is involved.

Results in humans demonstrate that fenoprofen has both anti-inflammatory and analgesic actions. The emergence and degree of erythemic response were measured in adult male volunteers exposed to ultraviolet irradiation. The effects of fenoprofen, aspirin and indomethacin were each compared with those of a placebo. All three drugs demonstrated antierythemic activity.

In all patients with rheumatoid arthritis, the anti-inflammatory action of NALFON has been evidenced by relief of pain, increase in grip strength and reductions in joint swelling, duration of morning stiffness and disease activity (as assessed by both the investigator and the patient). The anti-inflammatory action of NALFON has also been evidenced by increased mobility (i.e., a decrease in the number of joints having limited motion).

The use of NALFON in combination with gold salts or corticosteroids has been studied in patients with rheumatoid arthritis. The studies, however, were inadequate in demonstrating whether further improvement is obtained by adding NALFON to maintenance therapy with gold salts or steroids. Whether or not NALFON used in conjunction with partially effective doses of a corticosteroid has a “steroid-sparing” effect is unknown.

In patients with osteoarthritis, the anti-inflammatory and analgesic effects of NALFON have been demonstrated by reduction in tenderness as a response to pressure and reductions in night pain, stiffness, swelling and overall disease activity (as assessed by both the patient and the investigator). These effects have also been demonstrated by relief of pain with motion and at rest and increased range of motion in involved joints.

In patients with rheumatoid arthritis and osteoarthritis, clinical studies have shown fenoprofen to be comparable to aspirin in controlling the aforementioned measures of disease activity, but mild gastrointestinal reactions (nausea, dyspepsia) and tinnitus occurred less frequently in patients treated with fenoprofen than in aspirin-treated patients. It is not known whether fenoprofen calcium causes less peptic ulceration than does aspirin.

In patients with pain, the analgesic action of NALFON has produced a reduction in pain intensity, an increase in pain relief, improvement in total analgesia scores and a sustained analgesic effect.

Under fasting conditions, fenoprofen is rapidly absorbed and peak plasma levels of 50 mcg/mL are achieved within 2 hours after oral administration of 600 mg doses. Good dose proportionality was observed between 200 mg and 600 mg doses in fasting male volunteers. The plasma half-life is approximately 3 hours. About 90% of a single oral dose is eliminated within 24 hours as fenoprofen glucuronide and 4’ hydroxy-fenoprofen glucuronide, the major urinary metabolites of fenoprofen. Fenoprofen is highly bound (99%) to albumin.

The concomitant administration of antacid (containing both aluminum and magnesium hydroxide) does not interfere with absorption of NALFON.

There is less suppression of collagen-induced platelet aggregation with single doses of fenoprofen calcium than there is with aspirin.

INDICATIONS AND USAGE

Carefully consider the potential benefits and risks of NALFON tablets, USP and other treatment options before deciding to use NALFON tablets. Use the lowest effective dose for the shortest duration consistent with individual patient treatment goals (see WARNINGS).

NALFON tablets are indicated:

- For relief of mild to moderate pain in adults.
- For relief of the signs and symptoms of rheumatoid arthritis.
- For relief of the signs and symptoms of osteoarthritis.

CONTRAINDICATIONS

NALFON tablets are contraindicated in patients who have shown hypersensitivity to fenoprofen calcium.

NALFON tablets should not be given to patients who have experienced asthma, urticaria or allergic-type reactions after taking aspirin or other NSAIDs. Severe, rarely fatal, anaphylactic-like reactions to NSAIDs have been reported in such patients (see WARNINGS: Anaphylactoid Reactions,and PRECAUTIONS: Preexisting Asthma).

NALFON is contraindicated in the setting of coronary artery bypass graft (CABG) surgery (see WARNINGS).

NALFON is contraindicated in patients with a history of significantly impaired renal function (see WARNINGS: Advanced Renal Disease).

WARNINGS

Cardiovascular Effects

Cardiovascular Thrombotic Events

Clinical trials of several COX-2 selective and nonselective NSAIDs of up to 3 years duration have shown an increased risk of serious cardiovascular (CV) thrombotic events, including myocardial infarction (MI) and stroke, which can be fatal. Based on available data, it is unclear that the risk for CV thrombotic events is similar for all NSAIDs. The relative increase in serious CV thrombotic events over baseline conferred by NSAID use appears to be similar in those with and without known CV disease or risk factors for CV disease. However, patients with known CV disease or risk factors had a higher absolute incidence of excess serious CV thrombotic events, due to their increased baseline rate. Some observational studies found that this increased risk of serious CV thrombotic events began as early as the first weeks of treatment. The increase in CV thrombotic risk has been observed most consistently at higher doses.

To minimize the potential risk for an adverse CV event in NSAID-treated patients, use the lowest effective dose for the shortest duration possible. Physicians and patients should remain alert for the development of such events, throughout the entire treatment course, even in the absence of previous CV symptoms. Patients should be informed about the signs and/or symptoms of serious CV events and the steps to take if they occur.

There is no consistent evidence that concurrent use of aspirin mitigates the increased risk of serious CV thrombotic events associated with NSAID use. The concurrent use of aspirin and an NSAID, such as NALFON, increases the risk of serious gastrointestinal (GI) events (see GI WARNINGS).

Status Post Coronary Artery Bypass Graft (CABG) Surgery

Two large, controlled clinical trials of a COX-2 selective NSAID for the treatment of pain in the first 10 to 14 days following CABG surgery found an increased incidence of myocardial infarction and stroke. NSAIDs are contraindicated in the setting of CABG (see CONTRAINDICATIONS).

Post-MI Patients

Observational studies conducted in the Danish National Registry have demonstrated that patients treated with NSAIDs in the post-MI period were at increased risk of reinfarction, CV-related death, and all-cause mortality beginning in the first week of treatment. In this same cohort, the incidence of death in the first year post MI was 20 per 100 person years in NSAID-treated patients compared to 12 per 100 person years in non-NSAID exposed patients. Although the absolute rate of death declined somewhat after the first year post-MI, the increased relative risk of death in NSAID users persisted over at least the next 4 years of follow-up.

Avoid the use of NALFON tablets in patients with a recent MI unless the benefits are expected to outweigh the risk of recurrent CV thrombotic events. If NALFON tablets are used in patients with a recent MI, monitor patients for signs of cardiac ischemia.

Hypertension

NSAIDs, including NALFON, can lead to onset of new hypertension or worsening of preexisting hypertension, either of which may contribute to the increased incidence of CV events. Patients taking thiazides or loop diuretics may have impaired response to these therapies when taking NSAIDs. NSAIDs, including NALFON, should be used with caution in patients with hypertension. Blood pressure (BP) should be monitored closely during the initiation of NSAID treatment and throughout the course of therapy.

Heart Failure and Edema

The Coxib and traditional NSAID Trialists’ Collaboration meta-analysis of randomized controlled trials demonstrated an approximately 2-fold increase in hospitalizations for heart failure in COX-2 selective-treated patients and nonselective NSAID-treated patients compared to placebo-treated patients. In a Danish National Registry study of patients with heart failure, NSAID use increased the risk of MI, hospitalization for heart failure, and death.

Additionally, fluid retention and edema have been observed in some patients treated with NSAIDs. Use of fenoprofen calcium may blunt the CV effects of several therapeutic agents used to treat these medical conditions [e.g., diuretics, ACE inhibitors, or angiotensin receptor blockers (ARBs)] (see Drug Interactions).

Avoid the use of NALFON tablets in patients with severe heart failure unless the benefits are expected to outweigh the risk of worsening heart failure. If NALFON tablets are used in patients with severe heart failure, monitor patients for signs of worsening heart failure.

Gastrointestinal Effects

Risk of Ulceration, Bleeding and Perforation

NSAIDs, including NALFON tablets, can cause serious gastrointestinal (GI) adverse events including inflammation, bleeding, ulceration and perforation of the stomach, small intestine or large intestine, which can be fatal. These serious adverse events can occur at any time, with or without warning symptoms, in patients treated with NSAIDs. Only one in five patients, who develop a serious upper GI adverse event on NSAID therapy, is symptomatic. Upper GI ulcers, gross bleeding or perforation caused by NSAIDs occur in approximately 1% of patients treated for 3 to 6 months, and in about 2% to 4% of patients treated for one year. These trends continue with longer duration of use, increasing the likelihood of developing a serious GI event at some time during the course of therapy. However, even short-term therapy is not without risk.

NSAIDs should be prescribed with extreme caution in those with a prior history of ulcer disease or gastrointestinal bleeding. Patients with a prior history of peptic ulcer disease and/or gastrointestinal bleedingwho use NSAIDs have a greater than 10-fold increased risk for developing a GI bleed compared to patients with neither of these risk factors. Other factors that increase the risk for GI bleeding in patients treated with NSAIDs include concomitant use of oral corticosteroids or anticoagulants, longer duration of NSAID therapy, smoking, use of alcohol, older age and poor general health status. Most spontaneous reports of fatal GI events are in elderly or debilitated patients and therefore, special care should be taken in treating this population.

To minimize the potential risk for an adverse GI event in patients treated with a NSAID, the lowest effective dose should be used for the shortest possible duration. Patients and physicians should remain alert for signs and symptoms of GI ulceration and bleeding during NSAID therapy and promptly initiate additional evaluation and treatment if a serious GI adverse event is suspected. This should include discontinuation of the NSAID until a serious GI adverse event is ruled out. For high risk patients, alternate therapies that do not involve NSAIDs should be considered.

Renal Effects

Long-term administration of NSAIDs has resulted in renal papillary necrosis and other renal injury. Renal toxicity has also been seen in patients in whom renal prostaglandins have a compensatory role in the maintenance of renal perfusion. In these patients, administration of a nonsteroidal anti-inflammatory drug may cause a dose-dependent reduction in prostaglandin formation and, secondarily, in renal blood flow, which may precipitate overt renal decomposition. Patients at greatest risk of this reaction are those with impaired renal function, heart failure, liver dysfunction, those taking diuretics and ACE inhibitors and the elderly. Discontinuation of NSAID therapy is usually followed by recovery to the pretreatment state.

Advanced Renal Disease

No information is available from controlled clinical studies regarding the use of NALFON tablets in patients with advanced renal disease. Therefore, treatment with NALFON tablets is not recommended in patients with advanced renal disease (see CONTRAINDICATIONS).

Anaphylactoid Reactions

As with other NSAIDs, anaphylactoid reactions may occur in patients without known prior exposure to fenoprofen. NALFON tablets should not be given to patients with the aspirin triad. This symptom complex typically occurs in asthmatic patients who experience rhinitis with or without nasal polyps, or who exhibit severe, potentially fatal bronchospasm after taking aspirin or other NSAIDs (see CONTRAINDICATIONSand PRECAUTIONS: Preexisting Asthma). Emergency help should be sought in cases where an anaphylactoid reaction occurs.

Skin Reactions

NSAIDs, including NALFON tablets, can cause serious skin adverse events such as exfoliative dermatitis, Stevens-Johnson Syndrome (SJS) and toxic epidermal necrolysis (TEN), which can be fatal. These serious events may occur without warning. Patients should be informed about the signs and symptoms of serious skin manifestations and use of the drug should be discontinued at the first appearance of skin rash or any other sign of hypersensitivity.

Drug Reaction with Eosinophilia and Systemic Symptoms (DRESS) has been reported in patients taking NSAIDs such as NALFON tablets. Some of these events have been fatal or life-threatening. DRESS typically, although not exclusively, presents with fever, rash, lymphadenopathy, and/or facial swelling. Other clinical manifestations may include hepatitis, nephritis, hematological abnormalities, myocarditis, or myositis. Sometimes symptoms of DRESS may resemble an acute viral infection. Eosinophilia is often present. Because this disorder is variable in its presentation, other organ systems not noted here may be involved. It is important to note that early manifestations of hypersensitivity, such as fever or lymphadenopathy, may be present even though rash is not evident. If such signs or symptoms are present, discontinue NALFON tablets and evaluate the patient immediately.

Fetal Toxicity

Premature Closure of Fetal Ductus Arteriosus

Avoid use of NSAIDs, including NALFON tablets, in pregnant women at about 30 weeks gestation and later. NSAIDs including NALFON tablets, increase the risk of premature closure of the fetal ductus arteriosus at approximately this gestational age.

Oligohydramnios/Neonatal Renal Impairment

Use of NSAIDs, including NALFON tablets, at about 20 weeks gestation or later in pregnancy may cause fetal renal dysfunction leading to oligohydramnios and, in some cases, neonatal renal impairment. These adverse outcomes are seen, on average, after days to weeks of treatment, although oligohydramnios has been infrequently reported as soon as 48 hours after NSAID initiation. Oligohydramnios is often, but not always, reversible with treatment discontinuation. Complications of prolonged oligohydramnios may, for example, include limb contractures and delayed lung maturation. In some postmarketing cases of impaired neonatal renal function, invasive procedures such as exchange transfusion or dialysis were required.

If NSAID treatment is necessary between about 20 weeks and 30 weeks gestation, limit NALFON tablets use to the lowest effective dose and shortest duration possible. Consider ultrasound monitoring of amniotic fluid if NALFON tablets treatment extends beyond 48 hours. Discontinue Fenoprofen Calcium Tablets if oligohydramnios occurs and follow up according to clinical practice (see PRECAUTIONS; Pregnancy).

Ocular

Studies to date have not shown changes in the eyes attributable to the administration of NALFON tablets. However, adverse ocular effects have been observed with other anti-inflammatory drugs. Eye examinations, therefore, should be performed if visual disturbances occur in patients taking fenoprofen.

Central Nervous System

Caution should be exercised by patients whose activities require alertness if they experience CNS side effects while taking NALFON tablets.

Hearing

Since the safety of NALFON tablets has not been established in patients with impaired hearing, these patients should have periodic tests of auditory function during prolonged therapy with fenoprofen.

PRECAUTIONS

General

NALFON tablets cannot be expected to substitute for corticosteroids or to treat corticosteroid insufficiency. Abrupt discontinuation of corticosteroids may lead to disease exacerbation. Patients on prolonged corticosteroid therapy should have their therapy tapered slowly if a decision is made to discontinue corticosteroids.

The pharmacological activity of NALFON tablets in reducing inflammation may diminish the utility of these diagnostic signs in detecting complications of presumed noninfectious, painful conditions.

Hepatic Effects

Borderline elevations of one or more liver tests may occur in up to 15% of patients taking NSAIDs including NALFON tablets. These laboratory abnormalities may progress, may remain unchanged or may be transient with continuing therapy. Notable elevations of ALT or AST (approximately three or more times the upper limit of normal) have been reported in approximately 1% of patients in clinical trials with NSAIDs. In addition, rare cases of severe hepatic reactions, including jaundice and fatal fulminant hepatitis, liver necrosis and hepatic failure, some of them with fatal outcomes have been reported.

A patient with symptoms and/or signs suggesting liver dysfunction, or in whom an abnormal liver test has occurred, should be evaluated for evidence of the development of a more severe hepatic reaction while on therapy with NALFON tablets. If clinical signs and symptoms consistent with liver disease develop, or if systemic manifestations occur (e.g., eosinophilia, rash, etc.), NALFON tablets should be discontinued.

Hematological Effects

Anemia is sometimes seen in patients receiving NSAIDs, including NALFON tablets. This may be due to fluid retention, occult or gross GI blood loss or an incompletely described effect upon erythropoiesis. Patients on long-term treatment with NSAIDs, including NALFON tablets, should have their hemoglobin or hematocrit checked if they exhibit any signs or symptoms of anemia. NSAIDs inhibit platelet aggregation and have been shown to prolong bleeding time in some patients. Unlike aspirin, their effect on platelet function is quantitatively less, of shorter duration, and reversible. Patients receiving NALFON tablets who may be adversely affected by alterations in platelet function, such as those with coagulation disorders or patients receiving anticoagulants, should be carefully monitored.

Preexisting Asthma

Patients with asthma may have aspirin-sensitive asthma. The use of aspirin in patients with aspirin-sensitive asthma has been associated with severe bronchospasm which can be fatal. Since cross-reactivity, including bronchospasm, between aspirin and other nonsteroidal anti-inflammatory drugs has been reported in such aspirin-sensitive patients, NALFON tablets should not be administered to patients with this form of aspirin sensitivity and should be used with caution in patients with preexisting asthma.

Information for Patients

Patients should be informed of the following information before initiating therapy with an NSAID and periodically during the course of ongoing therapy. Patients should also be encouraged to read the NSAID Medication Guide that accompanies each prescription dispensed.

1. Cardiovascular Thrombotic Events: Advise patients to be alert for the symptoms of cardiovascular thrombotic events, including chest pain, shortness of breath, weakness, or slurring of speech, and to report any of these symptoms to their healthcare provider immediately (see WARNINGS).
2. NALFON tablets, like other NSAIDs, can cause GI discomfort and, rarely, serious GI side effects, such as ulcers and bleeding, which may result in hospitalization and even death. Although serious GI tract ulcerations and bleeding can occur without warning symptoms, patients should be alert for the signs and symptoms of ulcerations and bleeding, and should ask for medical advice when observing any indicative sign or symptoms including epigastric pain, dyspepsia, melena and hematemesis. Patients should be apprised of the importance of this follow-up (see WARNINGS: Gastrointestinal Effects: Risk of Ulceration, Bleeding, and Perforation).
3. Serious Skin Reactions, including DRESS Advise patients to stop taking NALFON tablets immediately if they develop any type of rash or fever and to contact their healthcare provider as soon as possible (see WARNINGS).
4. Heart Failure and Edema: Advise patients to be alert for the symptoms of congestive heart failure including shortness of breath, unexplained weight gain, or edema and to contact their healthcare provider if such symptoms occur (see WARNINGS).
5. Patients should be informed of the warning signs and symptoms of hepatotoxicity (e.g., nausea, fatigue, lethargy, pruritus, jaundice, right upper quadrant tenderness and "flu- like" symptoms). If these occur, patients should be instructed to stop therapy and seek immediate medical therapy.
6. Patients should be informed of the signs of an anaphylactoid reaction (e.g. difficulty breathing, swelling of the face or throat). If these occur, patients should be instructed to seek immediate emergency help (see WARNINGS).
7. Fetal Toxicity Inform pregnant women to avoid use of NALFON tablets and other NSAIDs starting at 30 weeks gestation because of the risk of the premature closing of the fetal ductus arteriosus. If treatment with NALFON tablets is needed for a pregnant woman between about 20 to 30 weeks gestation, advise her that she may need to be monitored for oligohydramnios, if treatment continues for longer than 48 hours (see WARNINGS; Fetal Toxicity, PRECAUTIONS; Pregnancy).

Laboratory Tests

Because serious GI tract ulcerations and bleeding can occur without warning symptoms, physicians should monitor for signs or symptoms of GI bleeding. Patients on long-term treatment with NSAIDs, should have their CBC and a chemistry profile checked periodically. If clinical signs and symptoms consistent with liver or renal disease develop, systemic manifestations occur (e.g., eosinophilia, rash, etc.) or if abnormal liver tests persist or worsen, fenoprofen should be discontinued.

Drug Interactions

ACE Inhibitors

Reports suggest that NSAIDs may diminish the antihypertensive effect of ACE inhibitors. This interaction should be given consideration in patients taking NSAIDs concomitantly with ACE inhibitors.

Aspirin

The coadministration of aspirin decreases the biologic half-life of fenoprofen because of an increase in metabolic clearance that results in a greater amount of hydroxylated fenoprofen in the urine. Although the mechanism of interaction between fenoprofen and aspirin is not totally known, enzyme induction and displacement of fenoprofen from plasma albumin binding sites are possibilities. As with other NSAIDs, concomitant administration of NALFON tablets and aspirin is not generally recommended because of the potential of increased adverse effects.

Diuretics

Clinical studies, as well as post-marketing observations, have shown that NALFON tablets can reduce the natriuretic effect of furosemide and thiazides in some patients. This response has been attributed to inhibition of renal prostaglandin synthesis. During concomitant therapy with NSAIDs, the patient should be observed closely for signs of renal failure (see WARNINGS: Renal Effects), as well as to assure diuretic efficacy.

Lithium

NSAIDs have produced an elevation of plasma lithium levels and a reduction in renal lithium clearance. The mean minimum lithium concentration increased 15% and the renal clearance was decreased by approximately 20%. These effects have been attributed to inhibition of renal prostaglandin synthesis by the NSAID. Thus, when NSAIDs and lithium are administered concurrently, subjects should be observed carefully for signs of lithium toxicity.

Methotrexate

NSAIDs have been reported to competitively inhibit methotrexate accumulation in rabbit kidney slices. This may indicate that they could enhance the toxicity of methotrexate. Caution should be used when NSAIDs are administered concomitantly with methotrexate.

Warfarin

The effects of warfarin and NSAIDs on GI bleeding are synergistic, such that users of both drugs together have a risk of serious GI bleeding higher than users of either drug alone.

Phenobarbital

Chronic administration of phenobarbital, a known enzyme inducer, may be associated with a decrease in the plasma half-life of fenoprofen. When phenobarbital is added to or withdrawn from treatment, dosage adjustment of NALFON tablets may be required.

Plasma Protein Binding

In vitrostudies have shown that fenoprofen, because of its affinity for albumin, may displace from their binding sites other drugs that are also albumin bound, and this may lead to drug interactions. Theoretically, fenoprofen could likewise be displaced. Patients receiving hydantoins, sulfonamides or sulfonylureas should be observed for increased activity of these drugs and, therefore, signs of toxicity from these drugs.

Drug/Laboratory Test Interactions

Amerlex-M kit assay values of total and free triiodothyronine in patients receiving fenoprofen have been reported as falsely elevated on the basis of a chemical cross-reaction that directly interferes with the assay. Thyroid-stimulating hormone, total thyroxine and thyrotropin-releasing hormone response are not affected.

Carcinogenesis, Mutagenesis and Impairment of Fertility

Long-term studies in animals have not been conducted to evaluate the carcinogenic potential of NALFON. Studies have not been conducted to determine the effect of NALFON on mutagenicity or fertility.

Pregnancy

Risk Summary

Use of NSAIDs, including NALFON tablets, can cause premature closure of the fetal ductus arteriosus and fetal renal dysfunction leading to oligohydramnios and, in some cases, neonatal renal impairment. Because of these risks, limit dose and duration of NALFON tablets use between about 20 and 30 weeks of gestation, and avoid NALFON tablets use at about 30 weeks of gestation and later in pregnancy (see WARNINGS; Fetal Toxicity).

Premature Closure of Fetal Ductus Arteriosus

Use of NSAIDs, including NALFON tablets, at about 30 weeks gestation or later in pregnancy increases the risk of premature closure of the fetal ductus arteriosus.

Oligohydramnios/Neonatal Renal Impairment

Use of NSAIDs at about 20 weeks gestation or later in pregnancy has been associated with cases of fetal renal dysfunction leading to oligohydramnios, and in some cases, neonatal renal impairment.

Data from observational studies regarding other potential embryofetal risks of NSAID use in women in the first or second trimesters of pregnancy are inconclusive.

Reproductive studies conducted in rats and rabbits have not demonstrated evidence of developmental abnormalities when given daily oral doses of 50 or 100 mg/kg fenoprofen calcium, respectively (0.15 and 0.6 times the maximum human daily dose of 3200 mg based on body surface area comparisons). However, animal reproduction studies are not always predictive of human response.

Because of the known effects of nonsteroidal anti-inflammatory drugs on the fetal cardiovascular system (closure of ductus arteriosus), use during pregnancy (particularly late pregnancy) should be avoided.

Based on animal data, prostaglandins have been shown to have an important role in endometrial vascular permeability, blastocyst implantation, and decidualization. In animal studies, administration of prostaglandin synthesis inhibitors, such as fenoprofen, resulted in increased pre- and post-implantation loss. Prostaglandins also have been shown to have an important role in fetal kidney development. In published animal studies, prostaglandin synthesis inhibitors have been reported to impair kidney development when administered at clinically relevant doses.

The estimated background risk of major birth defects and miscarriage for the indicated population(s) is unknown. All pregnancies have a background risk of birth defect, loss, or other adverse outcomes. In the U.S. general population, the estimated background risk of major birth defects and miscarriage in clinically recognized pregnancies is 2-4% and 15-20%, respectively.

Clinical Considerations

Fetal/Neonatal Adverse Reactions

Premature Closure of Fetal Ductus Arteriosus:

Avoid use of NSAIDs in women at about 30 weeks gestation and later in pregnancy, because NSAIDs, including NALFON tablets, can cause premature closure of the fetal ductus arteriosus (see WARNINGS; Fetal Toxicity).

Oligohydramnios/Neonatal Renal Impairment:

If an NSAID is necessary at about 20 weeks gestation or later in pregnancy, limit the use to the lowest effective dose and shortest duration possible. If NALFON tablets treatment extends beyond 48 hours, consider monitoring with ultrasound for oligohydramnios. If oligohydramnios occurs, discontinue NALFON tablets and follow up according to clinical practice (see WARNINGS; Fetal Toxicity).

Data

Human Data

There are no adequate and well-controlled studies of in pregnant women.

Premature Closure of Fetal Ductus Arteriosus:

Published literature reports that the use of NSAIDs at about 30 weeks of gestation and later in pregnancy may cause premature closure of the fetal ductus arteriosus.

Oligohydramnios/Neonatal Renal Impairment:

Published studies and postmarketing reports describe maternal NSAID use at about 20 weeks gestation or later in pregnancy associated with fetal renal dysfunction leading to oligohydramnios, and in some cases, neonatal renal impairment. These adverse outcomes are seen, on average, after days to weeks of treatment, although oligohydramnios has been infrequently reported as soon as 48 hours after NSAID initiation. In many cases, but not all, the decrease in amniotic fluid was transient and reversible with cessation of the drug. There have been a limited number of case reports of maternal NSAID use and neonatal renal dysfunction without oligohydramnios, some of which were irreversible. Some cases of neonatal renal dysfunction required treatment with invasive procedures, such as exchange transfusion or dialysis.

Methodological limitations of these postmarketing studies and reports include lack of a control group; limited information regarding dose, duration, and timing of drug exposure; and concomitant use of other medications. These limitations preclude establishing a reliable estimate of the risk of adverse fetal and neonatal outcomes with maternal NSAID use. Because the published safety data on neonatal outcomes involved mostly preterm infants, the generalizability of certain reported risks to the full-term infant exposed to NSAIDs through maternal use is uncertain.

Labor and Delivery

The effects of NALFON tablets on labor and delivery in pregnant women are unknown. In rat studies, maternal exposure to NSAIDs, as with other drugs known to inhibit prostaglandin synthesis, increased the incidence of dystocia, delayed parturition and decreased pup survival.

Nursing Mothers

It is not known whether this drug is excreted in human milk. Because many drugs are excreted in human milk and because of the potential for serious adverse reactions in nursing infants from NALFON tablets, a decision should be made whether to discontinue nursing or to discontinue the drug, taking into account the importance of the drug to the mother.

Pediatric Use

Safety and effectiveness in pediatric patients below the age of 18 have not been established.

Geriatric Use

As with any NSAIDs, caution should be exercised in treating the elderly (65 years and older).

ADVERSE REACTIONS

During clinical studies for rheumatoid arthritis, osteoarthritis or mild to moderate pain and studies of pharmacokinetics, complaints were compiled from a checklist of potential adverse reactions, and the following data emerged. These encompass observations in 6,786 patients, including 188 observed for at least 52 weeks. For comparison, data are also presented from complaints received from the 266 patients who received placebo in these same trials. During short-term studies for analgesia, the incidence of adverse reactions was markedly lower than that seen in longer-term studies.

Adverse Drug Reactions Reported in ≥ 1% of Patients During Clinical Trials

Digestive System:During clinical trials with fenoprofen calcium, the most common adverse reactions were gastrointestinal in nature and occurred in 20.8% of patients receiving fenoprofen as compared to 16.9% of patients receiving placebo. In descending order of frequency, these reactions included dyspepsia (10.3% fenoprofen vs. 2.3% placebo), nausea (7.7% vs. 7.1%), constipation (7% vs. 1.5%), vomiting (2.6% vs. 1.9%), abdominal pain (2% vs. 1.1%) and diarrhea (1.8% vs. 4.1%). The drug was discontinued because of adverse gastrointestinal reactions in less than 2% of patients during premarketing studies.

Nervous System:The most frequent adverse neurologic reactions were headache (8.7% vs. 7.5%) and somnolence (8.5% vs. 6.4%). Dizziness (6.5% vs. 5.6%), tremor (2.2% vs. 0.4%) and confusion (1.4% vs. none) were noted less frequently. Fenoprofen was discontinued in less than 0.5% of patients because of these side effects during premarketing studies.

Skin and Appendages:Increased sweating (4.6% vs. 0.4%), pruritus (4.2% vs. 0.8%) and rash (3.7% vs. 0.4%) were reported. Fenoprofen was discontinued in about 1% of patients because of an adverse effect related to the skin during premarketing studies.

Special Senses:Tinnitus (4.5% vs. 0.4%), blurred vision (2.2% vs. none) and decreased hearing (1.6% vs. none) were reported. Fenoprofen was discontinued in less than 0.5% of patients because of adverse effects related to the special senses during premarketing studies.

Cardiovascular:Palpitations (2.5% vs. 0.4%). Fenoprofen was discontinued in about 0.5% of patients because of adverse cardiovascular reactions during premarketing studies.

Miscellaneous:Nervousness (5.7% vs. 1.5%), asthenia (5.4% vs. 0.4%), peripheral edema (5% vs. 0.4%), dyspnea (2.8% vs. none), fatigue (1.7% vs. 1.5%), upper respiratory infection (1.5% vs. 5.6%) and nasopharyngitis (1.2% vs. none).

Adverse Drug Reactions Reported in < 1% of Patients During Clinical Trials

Digestive System:Gastritis, peptic ulcer with/without perforation, gastrointestinal hemorrhage, anorexia, flatulence, dry mouth and blood in the stool. Increases in alkaline phosphatase, LDH, SGOT, jaundice and cholestatic hepatitis, aphthous ulcerations of the buccal mucosa, metallic taste and pancreatitis (see PRECAUTIONS).

Cardiovascular:Atrial fibrillation, pulmonary edema, electrocardiographic changes and supraventricular tachycardia.

Genitourinary Tract:Renal failure, dysuria, cystitis, hematuria, oliguria, azotemia, anuria, interstitial nephritis, nephrosis and papillary necrosis (see WARNINGS).

Hyper sensitivity:Angioedema (angioneurotic edema).

Hematologic:Purpura, bruising, hemorrhage, thrombocytopenia, hemolytic anemia, aplastic anemia, agranulocytosis and pancytopenia.

Nervous System:Depression, disorientation, seizures and trigeminal neuralgia.

Special Senses:Burning tongue, diplopia and optic neuritis.

Skin and Appendages:Exfoliative dermatitis, toxic epidermal necrolysis, Stevens-Johnson Syndrome and alopecia.

Miscellaneous:Anaphylaxis, urticaria, malaise, insomnia, tachycardia, personality change, lymphadenopathy, mastodynia and fever.

OVERDOSAGE

Signs and Symptoms

Symptoms of overdose appear within several hours and generally involve the gastrointestinal and central nervous systems. They include dyspepsia, nausea, vomiting, abdominal pain, dizziness, headache, ataxia, tinnitus, tremor, drowsiness and confusion. Hyperpyrexia, tachycardia, hypotension and acute renal failure may occur rarely following overdose. Respiratory depression and metabolic acidosis have also been reported following overdose with certain NSAIDs.

Treatment

To obtain up-to-date information about the treatment of overdose, a good resource is your certified Regional Poison Control Center. Telephone numbers of certified poison control centers are listed in the Physicians' Desk Reference (PDR). In managing overdosage, consider the possibility of multiple drug overdoses, interaction among drugs and unusual drug kinetics in your patient.

Protect the patient's airway and support ventilation and perfusion. Meticulously monitor and maintain, within acceptable limits, the patient's vital signs, blood gases, serum electrolytes, etc. Absorption of drugs from the gastrointestinal tract may be decreased by giving activated charcoal, which, in many cases, is more effective than lavage; consider charcoal instead of or in addition to gastric emptying.
Repeated doses of charcoal over time may hasten elimination of some drugs that have been absorbed.Safeguard the patient's airway when employing gastric emptying or charcoal.

Alkalinization of the urine, forced diuresis, peritoneal dialysis, hemodialysis and charcoal hemoperfusion do not enhance systemic drug elimination.

DOSAGE AND ADMINISTRATION

Carefully consider the potential benefits and risks of NALFON tablets and other treatment options before deciding to use NALFON tablets. Use the lowest effective dose for the shortest duration consistent with individual patient treatment goals (see WARNINGS).

After observing the response to initial therapy with NALFON tablets, the dose and frequency should be adjusted to suit an individual patient's needs.

Analgesia

For the treatment of mild to moderate pain, the recommended dosage is 200 mg given orally every 4 to 6 hours, as needed.

Rheumatoid Arthritis and Osteoarthritis

For the relief of signs and symptoms of rheumatoid arthritis or osteoarthritis the recommended dose is 400 mg to 600 mg given orally, 3 or 4 times a day. The dose should be tailored to the needs of the patient and may be increased or decreased depending on the severity of the symptoms. Dosage adjustments may be made after initiation of drug therapy or during exacerbations of the disease. Total daily dosage should not exceed 3200 mg.

NALFON tablets may be administered with meals or with milk. Although the total amount absorbed is not affected, peak blood levels are delayed and diminished.

Patients with rheumatoid arthritis generally seem to require larger doses of NALFON tablets than do those with osteoarthritis. The smallest dose that yields acceptable control should be employed.

Although improvement may be seen in a few days in many patients, an additional 2 to 3 weeks may be required to gauge the full benefits of therapy.

HOW SUPPLIED

NALFON (fenoprofen calcium tablets), USP are available containing fenoprofen calcium, USP equivalent to 600 mg fenoprofen.

The 600 mg tablet is an orange film-coated, capsule-shaped tablet debossed with "600"on one side of the tablet and scored on the other side.

They are available as follows:

NDC 82804-129-90

bottles of 90 tablets

Store at 20° to 25°C (68° to 77°F). [See USP Controlled Room Temperature.]

Protect from light.

Dispense in a tight, light-resistant container as defined in the USP using a child-resistant closure.

PHARMACIST:Dispense a Medication Guide with each prescription.

Medication Guide for Nonsteroidal Anti-inflammatory Drugs (NSAIDs)

What is the most important information I should know about medicines called Nonsteroidal Anti-inflammatoryDrugs (NSAIDs)?

NSAIDs can cause serious side effects, including:

- Increased risk of a heart attack or stroke that can lead to death.This risk may happen early in treatment and may increase:
  - with increasing doses of NSAIDs
  - with longer use of NSAIDs

Do not take NSAIDs right before or after a heart surgery called a “coronary artery bypass graft (CABG)."
Avoid taking NSAIDs after a recent heart attack, unless your healthcare provider tells you to. You may have an increased risk of another heart attack if you take NSAIDs after a recent heart attack .

- Increased risk of bleeding, ulcers, and tears (perforation) of the esophagus (tube leading from the mouth to the stomach), stomach and intestines:
  - anytime during use
  - without warning symptoms
  - that may cause death
- The risk of getting an ulcer or bleeding increases with:
  - past history of stomach ulcers, or stomach or intestinal bleeding with use of NSAID
  - taking medicines called “corticosteroids”, “anticoagulants”, “SSRIs”, or “SNRIs”
  - increasing doses of NSAIDs
  - older age
  - longer use of NSAIDs
  - poor health
  - smoking
  - advanced liver disease
  - drinking alcohol
  - bleeding problems
- NSAIDs should only be used:
  - exactly as prescribed
  - at the lowest dose possible for your treatment
  - for the shortest time needed

What are NSAIDs?

NSAIDs are used to treat pain and redness, swelling, and heat (inflammation) from medical conditions such as different types of arthritis, menstrual cramps, and other types of short-term pain.

Who should not take NSAIDs?

Do not take NSAIDs:

- if you have had an asthma attack, hives, or other allergic reaction with aspirin or any other NSAIDs.
- right before or after heart bypass surgery.

Before taking NSAIDs, tell your healthcare provider about all of your medical conditions, including if you:

- have liver or kidney problems
- have high blood pressure
- have asthma
- are pregnant or plan to become pregnant. Taking NSAIDs at about 20 weeks of pregnancy or later may harm your unborn baby. If you need to take NSAIDs for more than 2 days when you are between 20 and 30 weeks of pregnancy, your healthcare provider may need to monitor the amount of fluid in your womb around your baby. You should not take NSAIDs after about 30 weeks of pregnancy.
- are breastfeeding or plan to breast feed.

Tell your healthcare provider about all of the medicines you take, including prescription or over-the- counter medicines, vitamins or herbal supplements.NSAIDs and some other medicines can interact with each other and cause serious side effects. Do not start taking any new medicine without talking to your healthcare provider first.

What are the possible side effects of NSAIDs?

NSAIDs can cause serious side effects, including:

See “What is the most important information I should know about medicines called Nonsteroidal Anti-inflammatory Drugs (NSAIDs)?

- new or worse high blood pressure
- heart failure
- liver problems including liver failure
- kidney problems including kidney failure
- low red blood cells (anemia)
- life-threatening skin reactions
- life threatening allergic reactions
- Other side effects of NSAIDs include:stomach pain, constipation, diarrhea, gas, heartburn, nausea, vomiting, and dizziness.

Get emergency help right away if you get any of the following symptoms:

- shortness of breath or trouble breathing
- slurred speech
- chest pain
- swelling of the face or throat
- weakness on one side of your body

Stop taking your NSAID and call your healthcare provider right away if you get any of the following symptoms:

- nausea
- vomit blood
- more tired or weaker than usual
- there is blood in your bowel movement or it is black and sticky like tar
- diarrhea
- itching
- unusual weight gain
- your skin or eyes look yellow
- skin rash or blisters with fever
- indigestion or stomach pain
- swelling of the arms, legs, hands and feet
- flu-like symptoms

If you take too much of your NSAID, call your healthcare provider or get medical help right away.
These are not all the possible side effects of NSAIDs. For more information, ask your healthcare provider or pharmacist about NSAIDs.

Call your doctor for medical advice about side effects . You may report side effects to FDA at 1-800-FDA-1088.

Other information about NSAIDs

- Aspirin is an NSAID but it does not increase the chance of a heart attack. Aspirin can cause bleeding in the brain, stomach, and intestines. Aspirin can also cause ulcers in the stomach and intestines.
- Some NSAIDs are sold in lower doses without a prescription (over-the-counter). Talk to your healthcare provider before using over-the-counter NSAIDs for more than 10 days.

General information about the safe and effective use of NSAIDs

Medicines are sometimes prescribed for purposes other than those listed in a Medication Guide. Do not use NSAIDs for a condition for which it was not prescribed. Do not give NSAIDs to other people, even if they have the same symptoms that you have. It may harm them.
If you would like more information about NSAIDs, talk with your healthcare provider. You can ask your pharmacist or healthcare provider for information about NSAIDs that is written for health professionals.

Manufactured for: Xspire Pharma, LLC, Ridgeland, MS, 39157 U.S.A.
For more information, call Xspire Pharma, LLC at 1-601-990-9497.

Repackaged by: Proficient Rx LP Thousand Oaks, CA 91320

This Medication Guide has been approved by the U.S. Food and Drug Administration.

Xspire Pharma LLC.
Ridgeland, MS 39157 U.S.A.

Repackaged by:

Proficient Rx LP
Thousand Oaks, CA 91320

REVISED APRIL 2021

Rx only

Keep container tightly closed.

Keep this and all medication out of the reach of children.

Protect from light.

Usual Adult Dosage:See accompanying prescribing information.

PACKAGING

Rx only

Keep container tightly closed.

Keep this and all medication out of the reach of children.

Protect from light.

Usual Adult Dosage:See accompanying prescribing information.